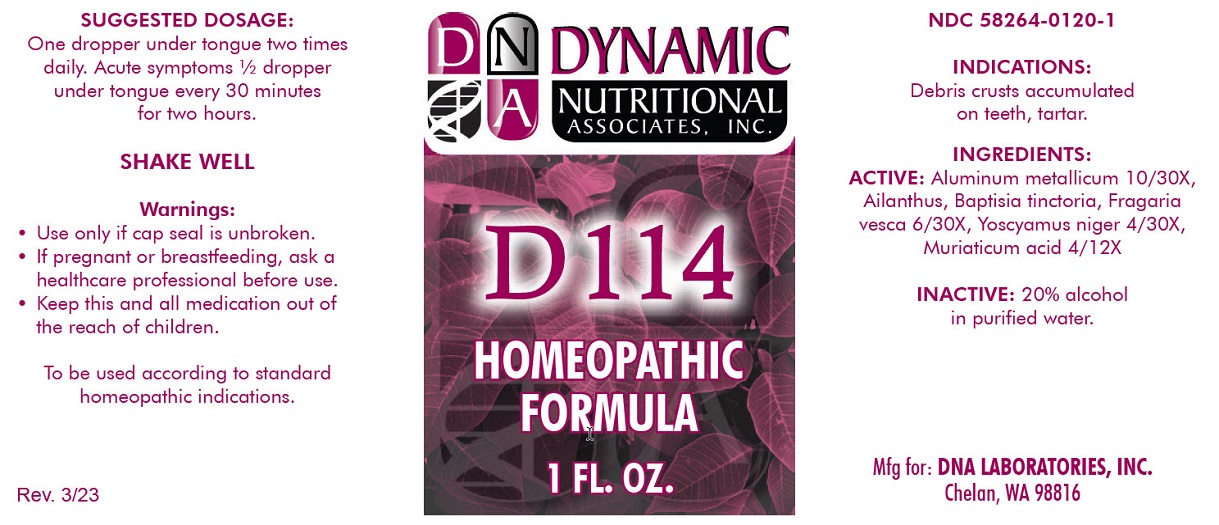 DRUG LABEL: D-114
NDC: 58264-0120 | Form: SOLUTION
Manufacturer: DNA Labs
Category: homeopathic | Type: HUMAN OTC DRUG LABEL
Date: 20250113

ACTIVE INGREDIENTS: ALUMINUM 30 [hp_X]/1 mL; AILANTHUS ALTISSIMA FLOWERING TWIG 30 [hp_X]/1 mL; HYOSCYAMUS NIGER 30 [hp_X]/1 mL; HYDROCHLORIC ACID 12 [hp_X]/1 mL; BAPTISIA TINCTORIA ROOT 30 [hp_X]/1 mL; FRAGARIA VESCA FRUIT 30 [hp_X]/1 mL
INACTIVE INGREDIENTS: ALCOHOL; WATER

D-114

NDC 58264-0120-1

INDICATIONS AND USAGE

PURPOSE

Debris crusts accumulated on teeth, tartar.

INGREDIENTS

ACTIVE

AlumInum metallicum 10/30X, Ailanthus, Baptisia tinctoria, Fragaria vesca 6/30X, Yoscyamus niger 4/30X, Muriaticum acid 4/12X

INACTIVE

20% alcohol in purified water.

SUGGESTED DOSAGE

One dropper under tongue two times daily. Accute symptoms 1/2 dropper under tongue every 30 minutes for two hours.

STORAGE AND HANDLING

SHAKE WELL

WARNINGS

- Use only if cap seal is unbroken.

PREGNANCY OR BREAST FEEDING

- If pregnant or breastfeeding, ask a healthcare professional before use.

KEEP OUT OF REACH OF CHILDREN

- Keep this and all medication out of the reach of children.

To be used according to standard homeopathic indications.

PRINCIPAL DISPLAY PANEL - 1 FL. OZ. - Bottle Label

DYNAMIC

NUTRITIONAL

ASSOCIATES, INC.

D-114

HOMEOPATHIC

1 FL. OZ.